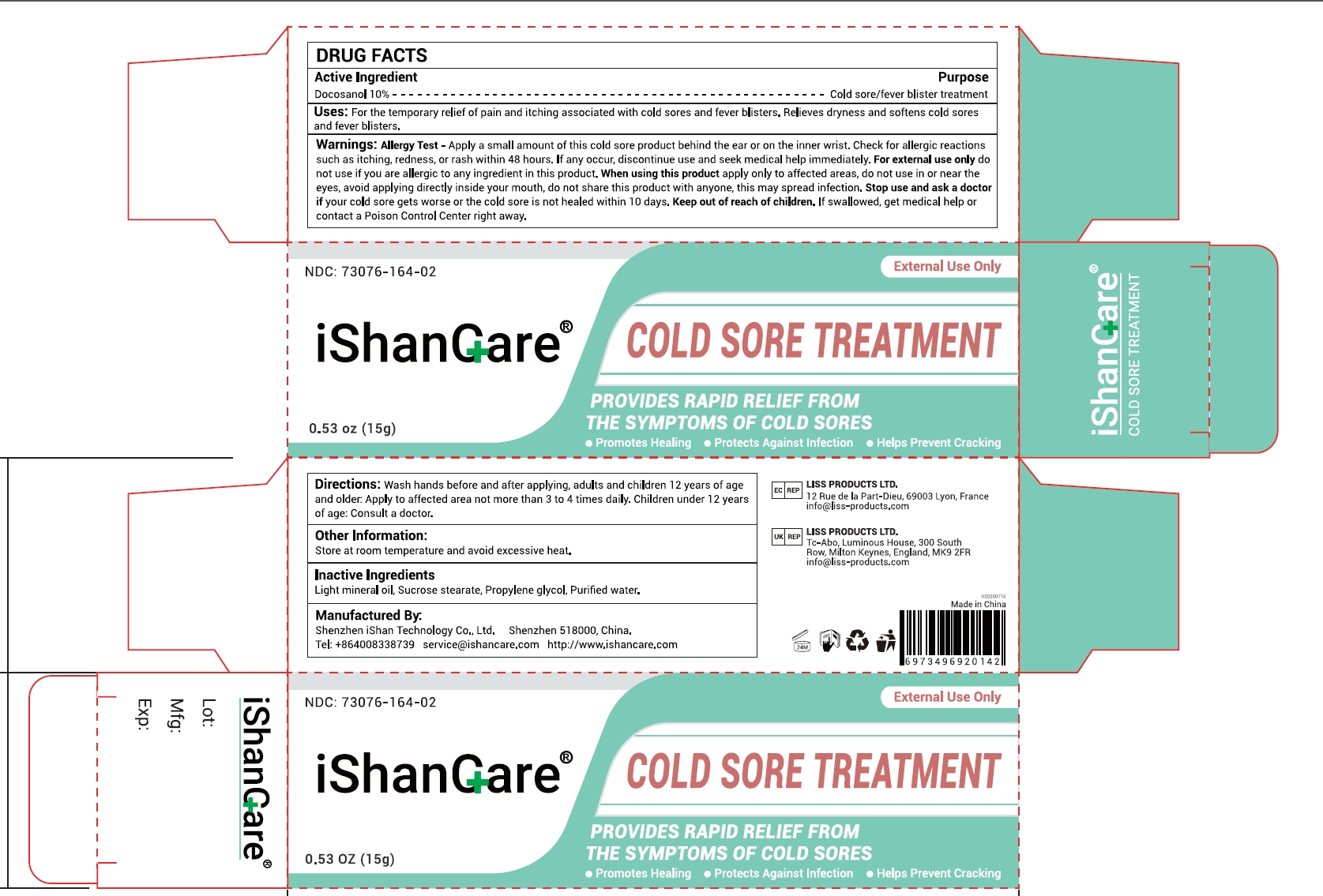 DRUG LABEL: iShanCare COLD SORE TREATMENT
NDC: 73076-164 | Form: GEL
Manufacturer: Shenzhen Ishan Technology Co., Ltd
Category: otc | Type: HUMAN OTC DRUG LABEL
Date: 20260212

ACTIVE INGREDIENTS: DOCOSANOL 10 g/100 g
INACTIVE INGREDIENTS: TARTARIC ACID; SUCROSE STEARATE; PROPYLENE GLYCOL 2-STEARATE; WATER

Active ingredients

Docosanol 10%-------------Cold sore / fever blister treatment

Inactive Ingredients

Light mineral oil, Sucrose stearate, Propylene glycol, Purified water.

Uses

For the temporary relief of pain and itching associated with cold sores and fever blisters. Relieves dryness and softens cold sores and fever blisters.

Warnings

Allergy Test-Apply a small amount of this cold sore product behind the ear or on the inner wrist.Check for allergic reactionssuch as itching,redness,orrash within 48hours.If any occur, discontinue use and seek medical help immediately.For external use only do
not useif you are allergic to anyingredient in this product.

When using this product

apply only to affected areas, do not use in or near theeyes, avoid applying directly inside your mouth, do not share this product with anyone, this may spread infection.

Stop use

if your cold sore gets worse or the cold soreis not healed within 10 days.

Ask a doctor

if your cold sore gets worse or the cold soreis not healed within 10 days.

Keep out of reach of children

If swallowed, get medical help or contact a Poison Control Center right away.

Dosage and administration

Wash hands before and after applying, adults and children12 years of age
and older: Apply to affected area not more than 3 to 4 times daily. Children under 12 years
of age: Consult a doctor.

Other information

Store a troom temperature and avoid excessive heat

Directions:

Wash hands before and after applying, adults and children12 years of age and older: Apply to affected area not more than 3 to 4 times daily. Children under 12 years of age: Consult a doctor.